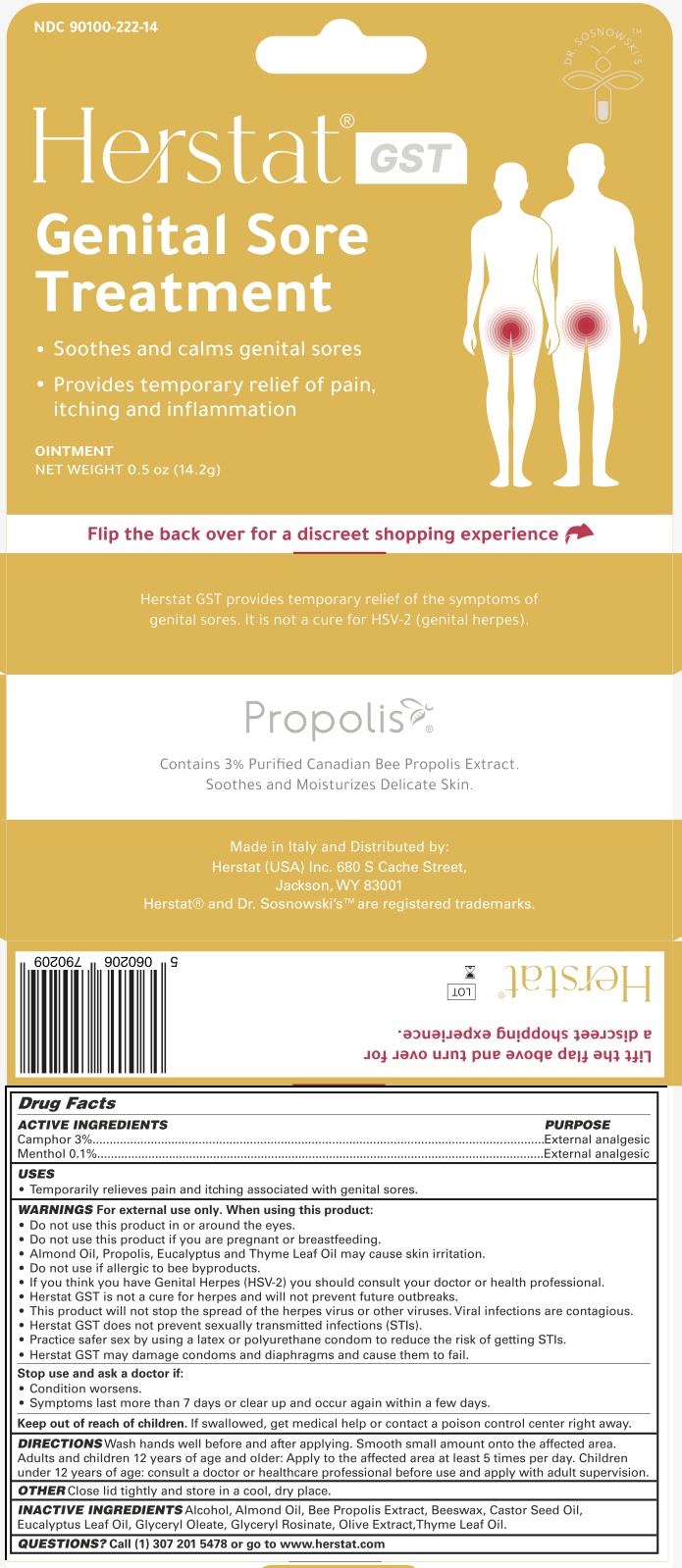 DRUG LABEL: HERSTAT GST Genital Sore Treatment
NDC: 90100-222 | Form: OINTMENT
Manufacturer: Herstat (USA) Inc.
Category: otc | Type: HUMAN OTC DRUG LABEL
Date: 20251219

ACTIVE INGREDIENTS: CAMPHOR (SYNTHETIC) 3 g/100 g; MENTHOL 0.1 g/100 g
INACTIVE INGREDIENTS: ALCOHOL; EUCALYPTUS OIL; ALMOND OIL; PROPOLIS WAX; THYME OIL; OLIVE OIL

HERSTAT GST Genital Sore Treatment

ACTIVE INGREDIENTS

Camphor 3%

Menthol 0.1%

PURPOSE

External analgesic

USES

Temporarily relieves pain and itching associated with genital sores.

WARNINGS

For external use only.

When using this product:

- Do not use in or around the eyes.
- Do not use this product if you are pregnant or breastfeeding
- Almond Oil, Propolis, Eucalyptus and Thyme Oil may cause skin irritation.
- Do not use if allergic to bee byproducts.
- If you think you have Genital Herpes (HSV-2) you should consult your doctor or health professional.
- Herstat GST is not a cure for herpes and will not prevent future outbreaks.
- This product will not stop the spread of the herpes virus or other viruses. Viral infections are contagious.
- Herstat GST does not prevent sexually transmitted infections (STIs).
- Practice safer sex by using a latex or polyurethane condom to reduce the risk of getting STIs.
- Herstat GST may damage comdoms and diaphragms and cause them to fail.

Stop use and ask a doctor if:

• Condition worsens.
• Symptoms last more than 7 days or clear up and occur again within a few days.

Keep out of reach of children.

If swallowed, get medical help or contact a poison control center right away.

DIRECTIONS

Wash hands well before and after applying. Smooth a small amount onto the affected area. Adults and children 12 years of age and older: Apply to the affected area at least 5 times per day.

Children under 12 years of age: consult a doctor or healthcare professional before use and under adult supervision.

OTHER

Close lid tightly and store in a cool, dry place.

INACTIVE INGREDIENTS

Alcohol, Almond Oil, Bees Propolis Extract, Eucalyptus Leaf Oil, Olive Extract, Thyme Leaf Oil.

QUESTIONS?

Questions? Call (1) 307 201 5478 or go to www.herstat.com

Principal Display Panel

Herstat®

Herstat Genital Sore Treatment

0.5 OZ (14.2g) Net Weight